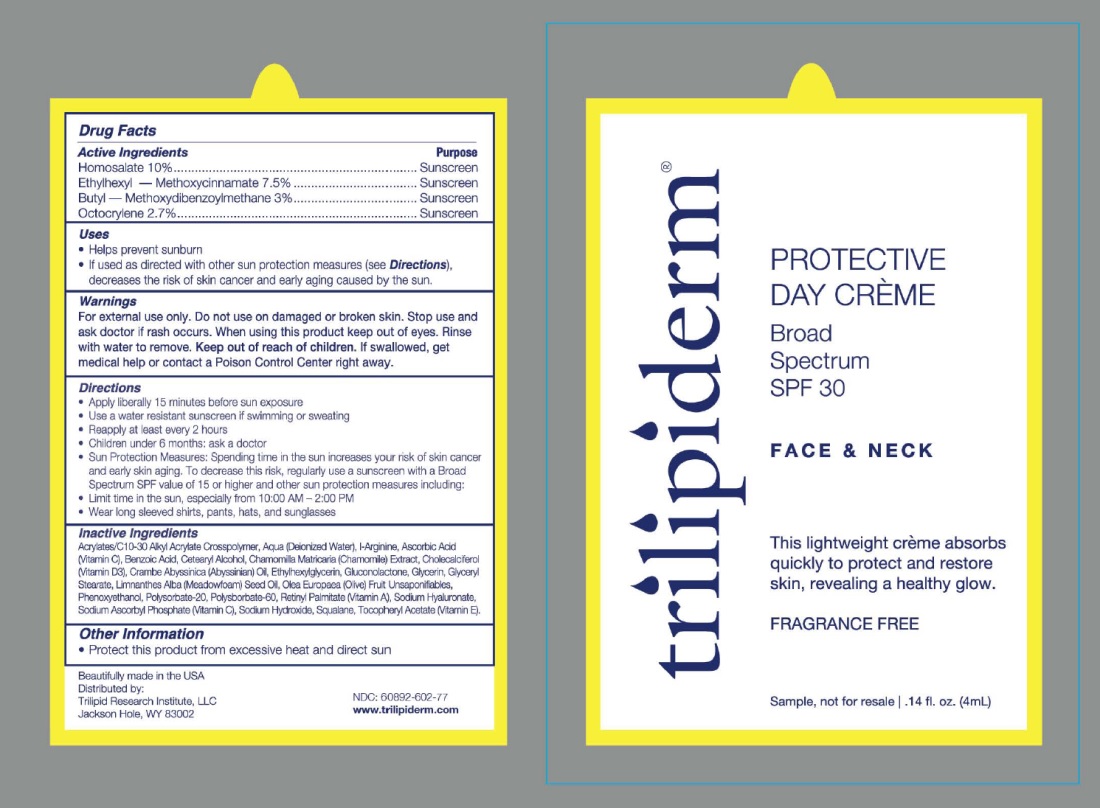 DRUG LABEL: TriLipiderm
NDC: 60892-602 | Form: CREAM
Manufacturer: TriLipid Research Institute, LLC
Category: otc | Type: HUMAN OTC DRUG LABEL
Date: 20251110

ACTIVE INGREDIENTS: OCTINOXATE 7.5 g/100 mL; AVOBENZONE 3 g/100 mL; HOMOSALATE 10 g/100 mL; OCTOCRYLENE 2.7 g/100 mL
INACTIVE INGREDIENTS: CRAMBE HISPANICA SUBSP. ABYSSINICA WHOLE; GLUCONOLACTONE; PHENOXYETHANOL; SQUALANE; SODIUM HYDROXIDE; ETHYLHEXYLGLYCERIN; GLYCERIN; GLYCERYL MONOSTEARATE; .ALPHA.-TOCOPHEROL ACETATE; ACRYLATES/C10-30 ALKYL ACRYLATE CROSSPOLYMER (60000 MPA.S); ASCORBIC ACID; CHOLECALCIFEROL; MEADOWFOAM SEED OIL; OLEA EUROPAEA (OLIVE) OIL UNSAPONIFIABLES; POLYSORBATE 60; BENZOIC ACID; CETOSTEARYL ALCOHOL; POLYSORBATE 20; CHAMOMILE; VITAMIN A; HYALURONATE SODIUM; SODIUM ASCORBYL PHOSPHATE; WATER; ARGININE

TriLipiderm Protective Day Creme

Active Ingredients

Homosalate 10%, Ethylhexyl Methoxycinnamate 7.5%, Butyl Methoxydibenzoylmethane 3%, Octocrylene 2.7%

Purpose

Sunscreen

Uses

- Helps Prevent Sunburn

- If used as directed with other sun protection measures (see Directions), decreases the risk of skin cancer and early skin aging caused by the sun.

Warnings

For external use only.

Do not use

on damaged or broken skin.

Stop use and ask a doctor

if rash occurs.

When using this product

Keep out of eyes. Rinse with water to remove

Keep out of reach of children.

If swallowed get medical help or contact a Poison Control Center right away

Directions:

- Apply liberally 15 minutes before sun exposure
- Use a water resistant sunscreen if swimming or sweating
- Reapply at least every 2 hours
- Children under 6 months: ask a doctor
- Sun Protection Measures. Spending time in the sun increases your risk of skin cancer and early skin aging. To decrease this risk, regularly use a sunscreen with a Broad Spectrum SPF value of 15 or higher and other sun protection measures including:
- Limit time in the sun, especially from 10:00 AM – 2:00 PM
- Wear long sleeved shirts, pants, hats, and sunglasses

Inactive Ingredients

Acrylates/C10-30 Alkyl Acrylate Crosspolymer, Aqua (Deionized Water), I-Arginine, Ascorbic Acid (Vitamin C), Benzoic Acid, Cetearyl Alcohol, Chamomilla Matricaria (Chamomile) Extract, Cholecalciferol (Vitamin D3), Crambe Abyssinica (Abyssinian) 0il, Ethylhexylglycerin, Gluconolactone, Glycerin, Glyceryl Stearate, Limnanthes Alba (Meadowfoam) Seed Oil, Olea Europaea (Olive) Fruit Unsaponifiables, Phenoxyethanol, Polysorbate-20, Polysorbate-60, Retinyl Palmitate (Vitamin A), Sodium Hyaluronate, Sodium Ascorbyl Phosphate (Vitamin C), Sodium Hydroxide, Squalane, Tocopheryl Acetate (Vitamin E)

Other Information

- Protect this product from excessive heat and direct sun